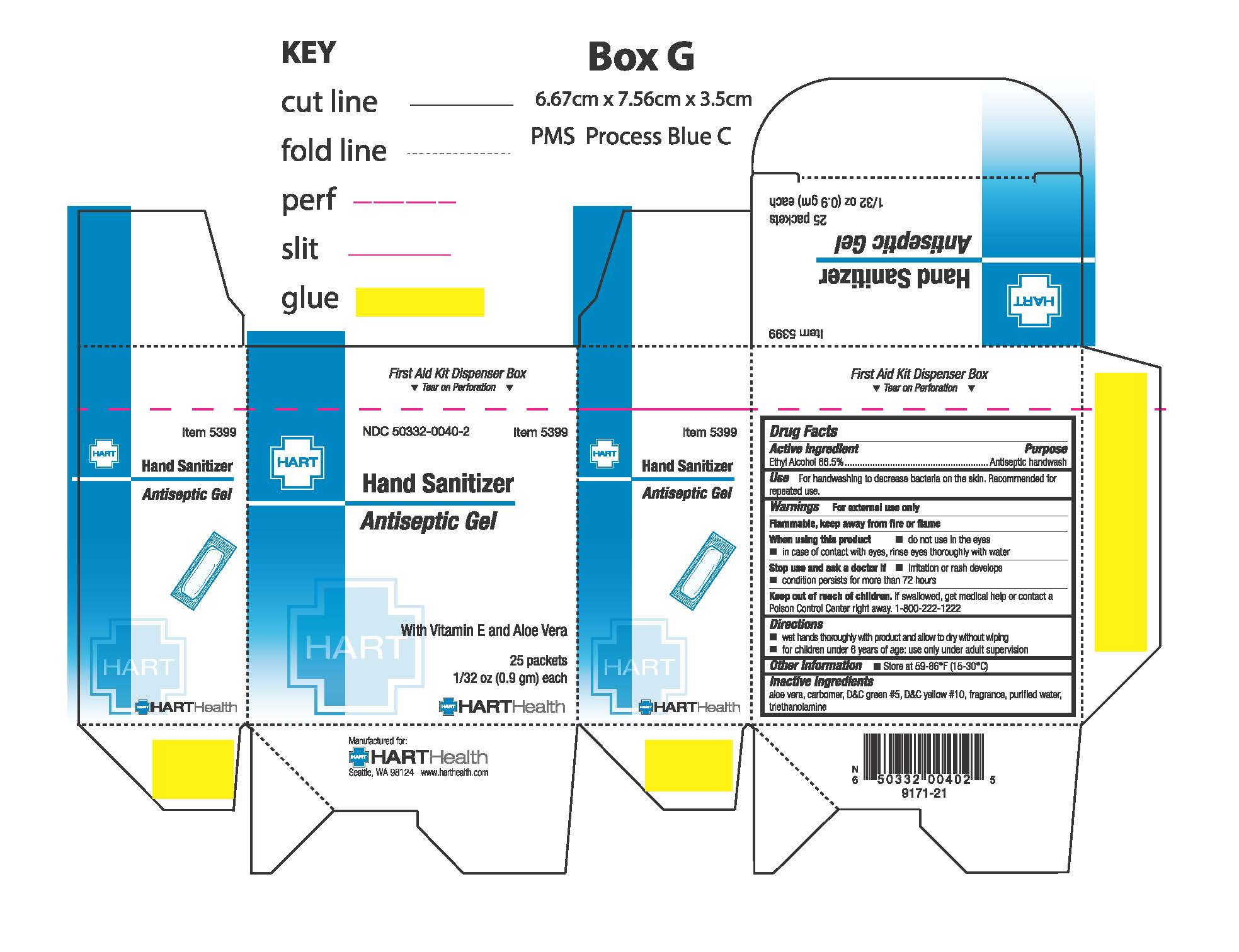 DRUG LABEL: Hand Sanitizer
NDC: 50332-0040 | Form: GEL
Manufacturer: HART Health
Category: otc | Type: HUMAN OTC DRUG LABEL
Date: 20240125

ACTIVE INGREDIENTS: ALCOHOL 62 g/100 g
INACTIVE INGREDIENTS: ALOE; D&C GREEN NO. 5; D&C YELLOW NO. 10; TROLAMINE; WATER

Hand Sanitizer Antiseptic Gel

Active Ingredients

Ethyl alcohol 62%

Purpose

Antiseptic handwash

Uses

For hanwashing to decrease bacteria on skin. Recommended for repeated use.

Warnings

For external use only

Flammable, keep away from heat and flame

When using this product

- do not use in the eyes
- in case of contact, rinse eyes throughly with water

Stop use and ask a doctor if

- irritation and redness develop
- condition persists for more than 72 hours

Keep out of reach of children

If swallowed get medical help or contact a Poison Control Center right away. 1-800-222-1222

Directions

- wet hands thoroughly with product and allow to dry without wiping
- for children under 6 years of age; use only with adult supervision

Inactive ingrediends

acrylates/C10-30 alkyl acrylate crosspolymer, aloe barbadensis leaf juice, fragrance, PEG-60 almond glycerides, propylene glycol, purified water, triisopropanolamine